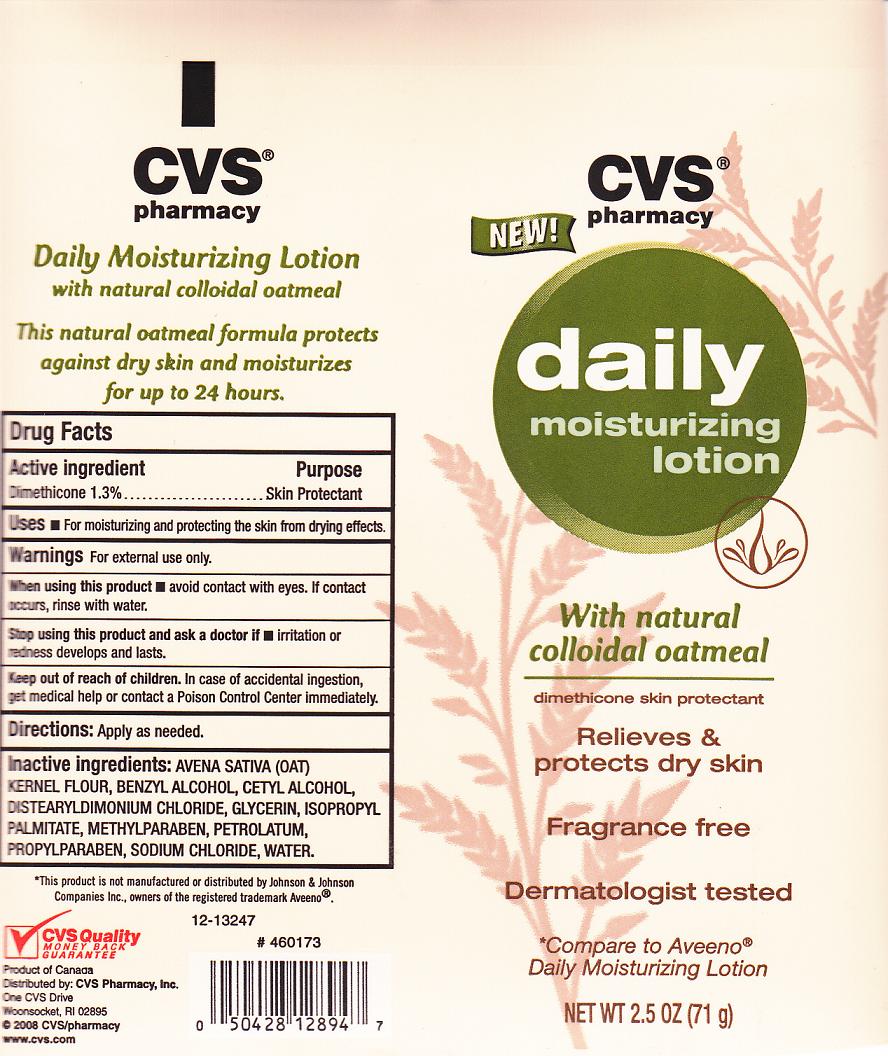 DRUG LABEL: CVS daily moisturizing 
NDC: 59779-323 | Form: LOTION
Manufacturer: CVS Pharmacy Inc
Category: otc | Type: HUMAN OTC DRUG LABEL
Date: 20101013

ACTIVE INGREDIENTS: DIMETHICONE 1.3 mL/100 mL

Drug Facts Box - Back Label

Active Ingredient

Dimethicone 1.3%

Purpose

Skin Protectant

Directions

Apply as needed

Warnings

- For external use only.

When using this product

Avoid contact with eyes. If contact occurs, rinse with water

Stop using this product and ask doctor if

irritation or redness develops and lasts

Keep out of reach of children

In case of accidental ingestion, get medical help or contact a Poison Control Center immediately

Uses

For moisturizing and protecting the skin from drying effects

Inactive Ingredients

Avena Sativa (oat) Kernel Flour, Benzyl Alcohol, Cetyl Alcohol, Distearyldimonium Chloride, Glycerin, Isopropyl Palmitate, Petrolatum, Sodium Chloride, Methylparaben, Propylparaben, Water.

Package Label

cvs2.5.jpg